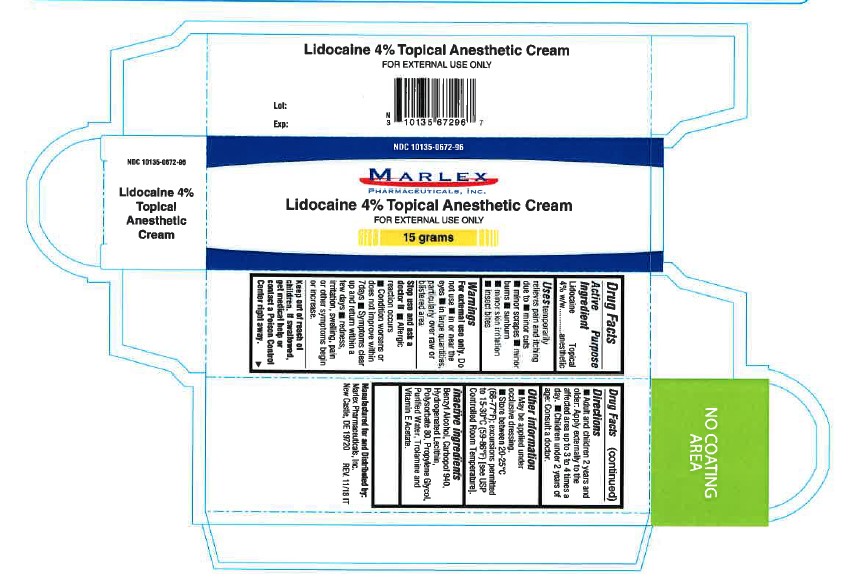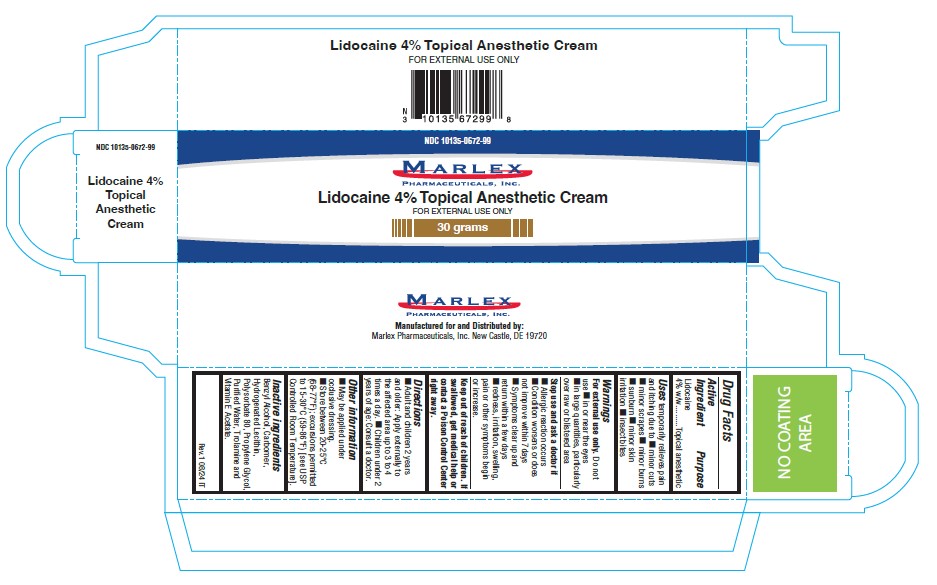 DRUG LABEL: Lidocaine
NDC: 10135-672 | Form: CREAM
Manufacturer: Marlex Pharmaceuticals Inc
Category: otc | Type: HUMAN OTC DRUG LABEL
Date: 20251114

ACTIVE INGREDIENTS: LIDOCAINE 40 mg/1 g
INACTIVE INGREDIENTS: BENZYL ALCOHOL; CARBOMER HOMOPOLYMER TYPE C (ALLYL PENTAERYTHRITOL CROSSLINKED); CHOLESTEROL; HYDROGENATED SOYBEAN LECITHIN; POLYSORBATE 80; PROPYLENE GLYCOL; ALPHA-TOCOPHEROL ACETATE; TROLAMINE; WATER

Lidocaine 4 Percent Topical Cream

LIDOCAINE 4%- lidocaine cream

Marlex Pharmaceuticals, Inc.

Disclaimer: Most OTC drugs are not reviewed and approved by FDA, however they may be marketed if they comply with applicable regulations and policies. FDA has not evaluated whether this product complies.

----------

Lidocaine 4% Topical

Drug Facts

Active ingredient

Lidocaine 4%

Purpose

Pain & Itch Relief

Use

for the temporary relief of pain associated with minor burns, sunburn, minor cuts, scrapes, insect bites, and minor skin irritations

Warnings

For external use only. Avoid contact with eyes. Not for prolonged use.

Donotusein large quantities, particularly over raw surfaces or blistered areas.

Stop use and ask a doctor if

- condition worsens
- symptoms persist for more than 7 days or clear up and occurs again within a few days
- rash or irritation develops, persists, or increases

If pregnant or breast-feeding,

ask a health professional before use.

Keep out of reach of children.

If swallowed, get medical help or contact a Poison Control Center right away

Directions

Adults and children 2 years of age and older:apply to affected area not more than 3 to 4 times daily

Children under 2 years of age:Consult a doctor

Other information

- May be applied under occlusive dressing
- store at 25°C (77°F); excursions permitted to 15-30°C (59-86°F)

Inactive ingredients

Benzyl alcohol, carbomer, hydrogenated lecithin, polysorbate 80, propylene glycol, purified water, trolamine and vitamin E acetate

PRINCIPAL DISPLAY PANEL- 15 g Tube Carton

Lidocaine 4% Topical Anesthetic Cream

Pain & Itch Relief Cream NET WT. 0.5 oz.(15g)

PRINCIPAL DISPLAY PANEL-30 g Tube Carton

Lidocaine 4% Topical Anesthetic Cream

Pain & Itch Relief Cream NET WT. (30g)